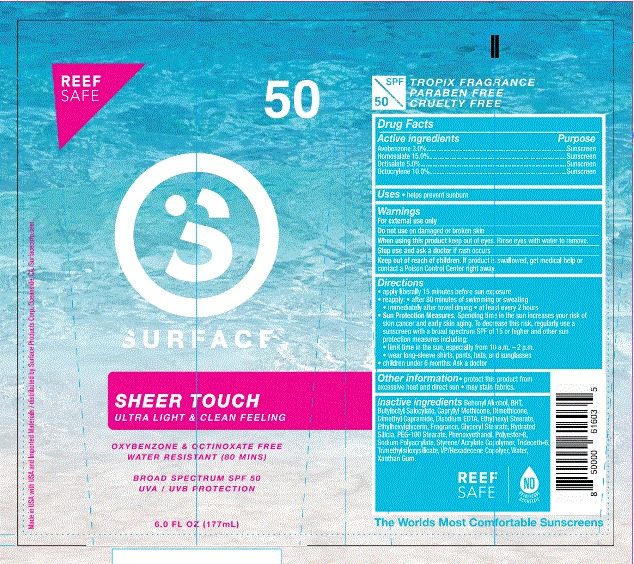 DRUG LABEL: Surface Sheer Touch SPF 50  with Fragrance
NDC: 72667-005 | Form: LOTION
Manufacturer: Inspec Solutions LLC.
Category: otc | Type: HUMAN OTC DRUG LABEL
Date: 20200310

ACTIVE INGREDIENTS: AVOBENZONE 3 g/100 mL; OCTOCRYLENE 10 g/100 mL; HOMOSALATE 15 g/100 mL; OCTISALATE 5 g/100 mL
INACTIVE INGREDIENTS: DIMETHYL CAPRAMIDE; COBALT DISODIUM EDETATE; DOCOSANOL; BUTYLOCTYL SALICYLATE; DIMETHICONE 20; ETHYLHEXYL STEARATE; ETHYLHEXYLGLYCERIN; GLYCERYL STEARATE CITRATE; SODIUM POLYACRYLATE (8000 MW); HYDRATED SILICA; PEG-100 STEARATE; PHENOXYETHANOL; TRIDECETH-6; XANTHAN GUM; VINYLPYRROLIDONE/HEXADECENE COPOLYMER; POLYESTER-8 (1400 MW, CYANODIPHENYLPROPENOYL CAPPED); STYRENE; TRIMETHYLSILOXYSILICATE (M/Q 0.6-0.8); WATER; 4-METHYL-1,4-PENTANEDIYL DIMETHACRYLATE

SURFACE SHEER TOUCH SPF 50 Sunscreen Lotion with FRAGRANCE

ACTIVE INGREDIENT

Avobenzone 3.0%

Homosalate 15.0%

Octisalate 5.0%

Octocrylene 10.0%

WARNINGS

For external use only.

Highly Flammable: Do not apply or use product near heat, flame, or while smoking.

When using this product:

• keep out of eyes. Rinse with water to remove.

• Keep away from face to avoid breathing it.

• Do not puncture or incinerate, Contents under pressure

• Do not store at temperature above 120⁰F

Stop use and ask a doctor if rash occurs.

Keep out of reach of children. If swallowed, get medical help or contact a Poison Control Center right away

INACTIVE INGREDIENT

Behenyl Alcohol

BHT

Butyloctyl Salocylate

Caprylyl Methicone

Dimethicone

Dimethyl Capramide

Disodium EDTA

Ethylhexyl Stearate

Ethylhexylglycerin

Fragrance

Glyceryl Stearate

Hydrated Silicia

PEG-100 Stearate

Phenoxyethanol

Polyester-8

Sodium Polyacrylate

Styrene/ Acrylate Copolymer

Trideceth-6

Trimethylsiloxysilicate

VP/Hexadecene Copolyer

Water

Xanthan Gum

Stop use and ask a doctor if rash occurs.

PURPOSE

Avobenzone 3.0% ..............................Sunscreen

Homosalate 15.0% .............................Sunscreen

Octisalate 5.0% ..................................Sunscreen

Octocrylene 10.0% .............................Sunscreen